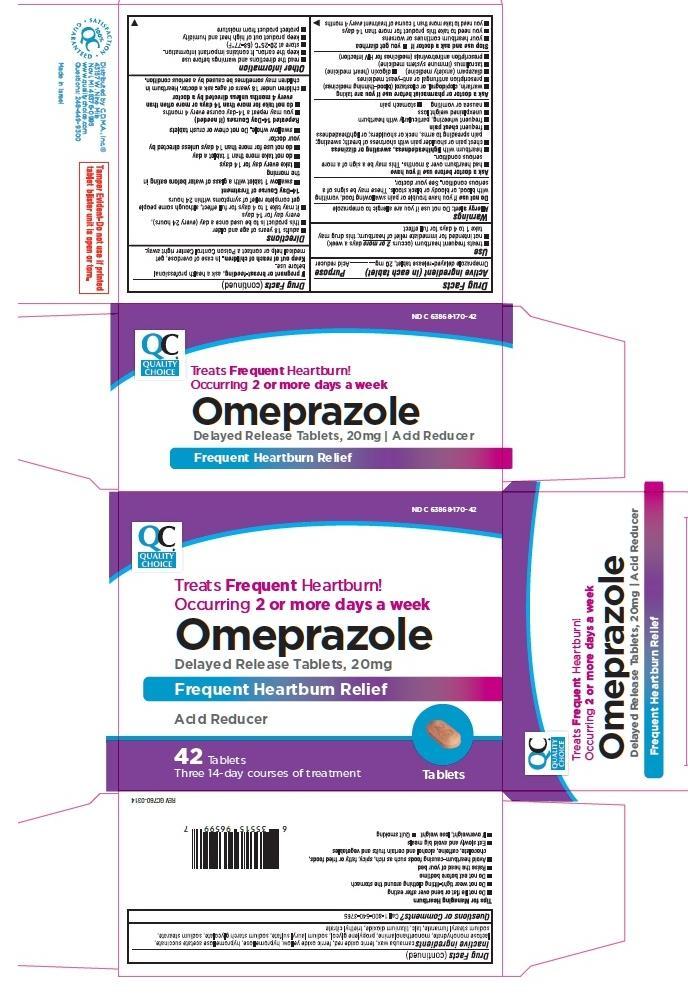 DRUG LABEL: QUALITY CHOICE OMEPRAZOLE 
                
NDC: 63868-170 | Form: TABLET, DELAYED RELEASE
Manufacturer: Chain Drug Marketing Association
Category: otc | Type: HUMAN OTC DRUG LABEL
Date: 20140522

ACTIVE INGREDIENTS: OMEPRAZOLE 20 mg/1 1
INACTIVE INGREDIENTS: CARNAUBA WAX; FERRIC OXIDE RED; FERRIC OXIDE YELLOW; HYPROMELLOSES; HYPROMELLOSE ACETATE SUCCINATE 12070923 (3 MM2/S); LACTOSE MONOHYDRATE; MONOETHANOLAMINE; PROPYLENE GLYCOL; SODIUM LAURYL SULFATE; SODIUM STARCH GLYCOLATE TYPE A POTATO; SODIUM STEARATE; SODIUM STEARYL FUMARATE; TALC; TITANIUM DIOXIDE; TRIETHYL CITRATE

Active ingredient (in each tablet)

Omeprazole delayed-release tablet, 20 mg

Purpose

Acid reducer

Use

- treats frequent heartburn (occurs 2 or more days a week)
- not intended for immediate relief of heartburn; this drug may take 1 to 4 days for full effect

Warnings

Allergy alert: Do not use if you are allergic to omeprazole

Do not use if you have trouble or pain swallowing food, vomiting with blood, or bloody or black stools. These may be signs of a serious condition. See your doctor.

Ask a doctor before use if you have

- had heartburn over 3 months. This may be a sign of a more serious condition.
- heartburn with lightheadedness, sweating or dizziness
- chest pain or shoulder pain with shortness of breath; sweating; pain spreading to arms, neck or shoulders; or lightheadedness
- frequent chest pain
- frequent wheezing, particularly with heartburn
- unexplained weight loss
- nausea or vomiting
- stomach pain

Ask a doctor or pharmacist before use if you are taking

- warfarin, clopidogrel or cilostazol (blood-thinning medicines)
- prescription antifungal or anti-yeast medicines
- diazepam (anxiety medicine)
- digoxin (heart medicine)
- tacrolimus (immune system medicine)
- prescription antiretrovirals (medicines for HIV infection)

Stop use and ask a doctor if

- your heartburn continues or worsens
- you need to take this product for more than 14 days
- you need to take more than 1 course of treatment every 4 months
- you get diarrhea

If pregnant or breast-feeding, ask a health professional before use.

Keep out of reach of children. In case of overdose, get medical help or contact a Poison Control Center right away.

Directions

- adults 18 years of age and older
- this product is to be used once a day (every 24 hours), every day for 14 days
- it may take 1 to 4 days for full effect, although some people get complete relief of symptoms within 24 hours

14-Day Course of Treatment

- swallow 1 tablet with a glass of water before eating in the morning
- take every day for 14 days
- do not take more than 1 tablet a day
- do not use for more than 14 days unless directed by your doctor
- swallow whole. Do not chew or crush tablets

Repeated 14-Day Courses (if needed)

- you may repeat a 14-day course every 4 months
- do not take for more than 14 days or more often than every 4 months unless directed by a doctor
- children under 18 years of age: ask a doctor. Heartburn in children may sometimes be caused by a serious condition.

Other information

- read the directions and warnings before use
- keep the carton. It contains important information.
- store at 20-25°C (68-77°F)
- keep product out of high heat and humidity
- protect product from moisture

Inactive ingredients

carnauba wax, ferric oxide red, ferric oxide yellow, hypromellose, hypromellose acetate succinate, lactose monohydrate, monoethanolamine, propylene glycol, sodium lauryl sulfate, sodium starch glycolate, sodium stearate, sodium stearyl fumarate, talc, titanium dioxide, triethyl citrate

Questions or comments?

Call 1-800-540-3765

Principal Display Panel

NDC 63868-170-42

QUALITY CHOICE

Treats Frequent Heartburn!

Occurring 2 or more days a week

Omeprazole

Delayed Release Tablets, 20mg

Frequent Heartburn Relief

Acid Reducer

42 Tablets

Three 14-day courses of treatment